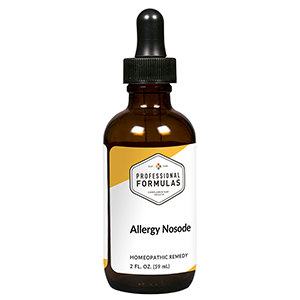 DRUG LABEL: Allergy Nosode
NDC: 63083-4017 | Form: LIQUID
Manufacturer: Professional Complementary Health Formulas
Category: homeopathic | Type: HUMAN OTC DRUG LABEL
Date: 20190815

ACTIVE INGREDIENTS: HOUSE DUST 12 [hp_X]/59 mL; STACHYBOTRYS CHARTARUM 12 [hp_X]/59 mL; MEDICAGO SATIVA WHOLE 12 [hp_X]/59 mL; FRAXINUS LATIFOLIA WHOLE 12 [hp_X]/59 mL; TARAXACUM OFFICINALE 12 [hp_X]/59 mL; POTASSIUM DICHROMATE 30 [hp_X]/59 mL; CALCIUM SULFIDE 12 [hp_X]/59 mL; HISTAMINE 12 [hp_X]/59 mL; SILICON DIOXIDE 12 [hp_X]/59 mL; GUAIAC 6 [hp_X]/59 mL; LUFFA OPERCULATA FRUIT 6 [hp_X]/59 mL
INACTIVE INGREDIENTS: ALCOHOL; WATER

N17

ACTIVE INGREDIENTS

House dust mix 12X (15% by volume)
Mold mix 12X (15% by volume)
Grass mix 12X (10% by volume)
Tree mix 12X (10% by volume)
Weed mix 12X (10% by volume)
Kali bichromicum 30X (5% by volume)
Hepar sulphuris calcareum 12X (5% by volume)
Histaminum 12X (5% by volume)
Silicea 12X (5% by volume)
Euphorbium officinalis 6X (5% by volume)
Guaiacum 6X (5% by volume)
Luffa operculata 6X (5% by volume)
Sinapsis nigra 3X (5% by volume)

QUESTIONS

Professional Formulas

PO Box 2034 Lake Oswego, OR 97035

INDICATIONS

For the temporary relief of runny nose, nasal congestion, headache, itchy or watery eyes, or mild facial or ear pain due to hay fever or other upper respiratory allergies.*

PURPOSE

*Claims based on traditional homeopathic practice, not accepted medical evidence. Not FDA evaluated.

WARNINGS

If symptoms do not improve or are accompanied by a fever, consult a doctor. Keep out of the reach of children. In case of overdose, get medical help or contact a poison control center right away. If pregnant or breastfeeding, ask a healthcare professional before use.

Keep out of the reach of children.

PREGNANCY OR BREAST FEEDING

If pregnant or breastfeeding, ask a healthcare professional before use.

DIRECTIONS

Place drops under tongue 30 minutes before/after meals. Adults and children 12 years and over: Take 10 to 15 drops once weekly or monthly. If mild symptoms are present, take 10 drops up to 3 times per day. Consult a physician for use in children under 12 years of age.

OTHER INFORMATION

Tamper resistant. If seal is broken, do not use. After opening, close container tightly and store at room temperature away from heat.

INACTIVE INGREDIENTS

20% ethanol, purified water.

LABEL

Est 1985

Professional Formulas

Complementary Health

Allergy Nosode

Homeopathic Remedy

2 FL. OZ. (59 mL)